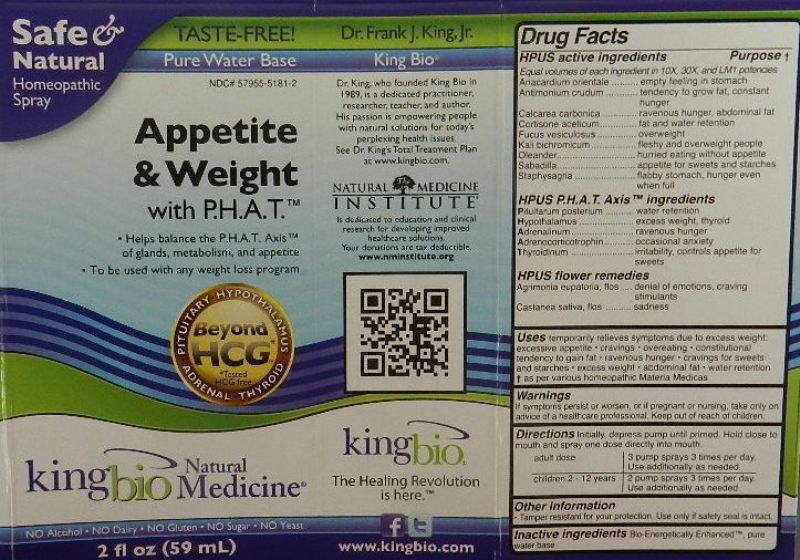 DRUG LABEL: Anxiety and Nervousness
NDC: 57955-5163 | Form: LIQUID
Manufacturer: King Bio Inc.
Category: homeopathic | Type: HUMAN OTC DRUG LABEL
Date: 20120220

ACTIVE INGREDIENTS: ACONITUM NAPELLUS 10 [hp_X]/59 mL; ALFALFA 10 [hp_X]/59 mL; SILVER NITRATE 10 [hp_X]/59 mL; ARSENIC TRIOXIDE 10 [hp_X]/59 mL; GOLD 10 [hp_X]/59 mL; AVENA SATIVA FLOWERING TOP 10 [hp_X]/59 mL; BARIUM CARBONATE 10 [hp_X]/59 mL; TRIBASIC CALCIUM PHOSPHATE 10 [hp_X]/59 mL; MATRICARIA RECUTITA 10 [hp_X]/59 mL; GELSEMIUM SEMPERVIRENS ROOT 10 [hp_X]/59 mL; NITROGLYCERIN 10 [hp_X]/59 mL; HOPS 10 [hp_X]/59 mL; STRYCHNOS IGNATII SEED 10 [hp_X]/59 mL; POTASSIUM ARSENITE ANHYDROUS 10 [hp_X]/59 mL; POTASSIUM PHOSPHATE, DIBASIC 10 [hp_X]/59 mL; HYDROCHLORIC ACID 10 [hp_X]/59 mL; SODIUM PHOSPHATE, DIBASIC, HEPTAHYDRATE 10 [hp_X]/59 mL; PASSIFLORA INCARNATA FLOWERING TOP 10 [hp_X]/59 mL; PHOSPHORUS 10 [hp_X]/59 mL; DELPHINIUM STAPHISAGRIA SEED 10 [hp_X]/59 mL; DATURA STRAMONIUM 10 [hp_X]/59 mL
INACTIVE INGREDIENTS: WATER

Anxiety and Nervousness

Active Ingredients

HPUS Active ingredients

Equal volumes of each ingredient in 10X, 30X and LM1 potencies.

Aconitum napellus

Alfalfa

Argentum nitricum

Arsenicum album

Aurum metallicum

Avena sativa

Baryta carbonica

Calcarea phosphorica

Chamomilla

Gelsemium sempervirens

Glonoinum

Humulus lupulus

Ignatia amara

Kali arsenicosum

Kali phosphoricum

Muriaticum acidum

Natrum phosphoricum

Passiflora incarnata

Phosphorus

Staphysagria

Stramonium

Reference image anxiety.jpg

Inactive Ingredient

Bio-Energetically Enhanced, taste-free, pure water base.

Reference image anxiety.jpg

Purpose

HPUS Active ingredients Purpose

Equal volumes of each ingredient in 10X, 30X and LM1 potencies.

Aconitum napellus.................................................fear, anxiety, inability to concentrate

Alfalfa..................................................................irritability, loss of appetite

Argentum nitricum................................................nervousness, impulsiveness, fear

Arsenicum album.................................................anguish, restlessness, oversensitivity

Aurum metallicum.................................................depression, grief, hopelessness

Avena sativa........................................................mental fatigue, sleeplessness, tremors

Baryta carbonica..................................................shyness, self-doubt

Calcarea phosphorica...........................................mental strain, forgetfulness

Chamomilla..........................................................impatience, irritability, agitation

Gelsemium sempervirens.....................................dizziness, fear, stage fright

Glonoinum...........................................................confusion, disorientation, irritability

Humulus lupulus..................................................nervous tremors, muscle twitching

Ignatia amara......................................................mood changes, oversensitivity

Kali arsenicosum.................................................anxiety, panic attacks, nervous stomach

Kali phosphoricum...............................................apprehensive, easily startled

Muriaticum acidum..............................................sadness, restlessness, irritability

Natrum phosphoricum.........................................easily frightened

Passiflora incarnata.............................................nervousness, sleeplessness

Phosphorus.........................................................anxiety, forgetfulness, apathy

Staphysagria.......................................................sadness, irritability, fear

Stramonium.........................................................mood swings, feelings of paranoia

Reference image anxiety.jpg

Dosage and Administration

Directions: Initially, depress pump until primed. Hold close to mouth and spray one dose directly into mouth.

Adult Dose 3 pump sprays 3 times per day. Use additionally as needed.

Children 2-12 years 2 pump sprays 3 times per day. Use additionally as needed.

Reference image anxiety.jpg

Warnings

Not intended as a substitute for standard medical care; intended to complement prescribed medication. If symptoms persist or worsen, seek advice of physician. If pregnant or nursing, take only on advice of physician.

Other Information:
Tamper resistant for your protection. Use only if safety seal is intact.

Reference image anxiety.jpg

Keep out of reach of children.

Reference image anxiety.jpg

Indications and Usage

Uses for temporary relief of symptoms:

- anxiety
- nervousness
- minor mood swings
- irritability
- restlessness
- stage fright
- nervous stomach
- for oversensitivity to darkness, sound, touch confusion, excitement or overwork

as per various homeopathic Materia Medicas.
Reference image anxiety.jpg

PACKAGE LABEL

King Bio Inc.

3 Westside Drive,

Asheville, NC 28806

Questions? Call 800.543.3245

www.kingbio.com

Safe and Natural Homeopathic Spray